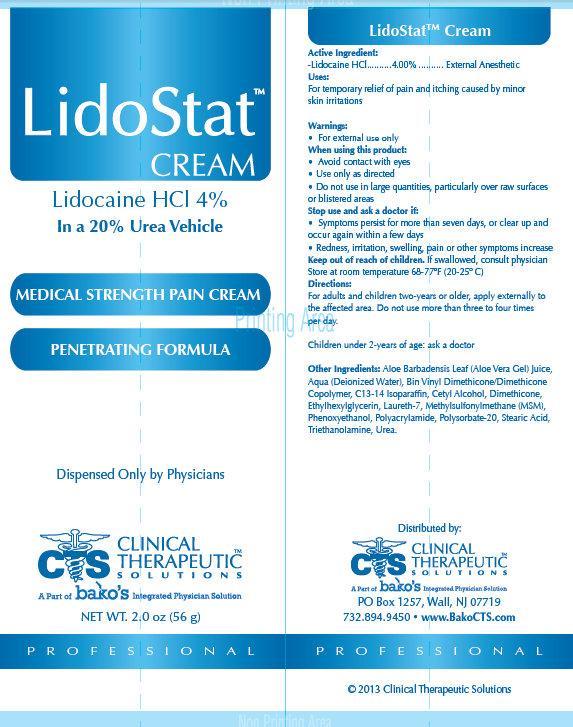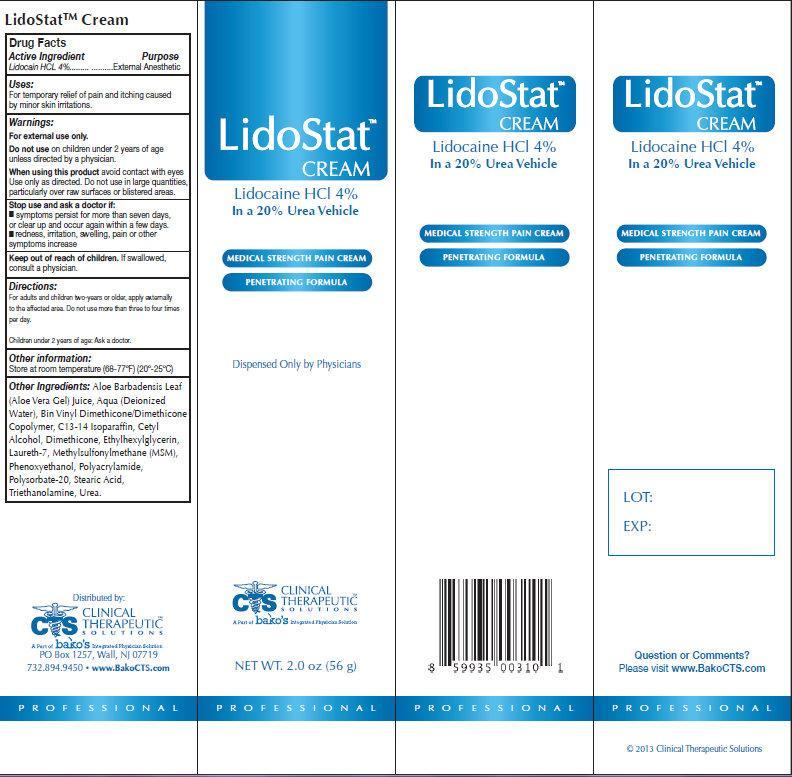 DRUG LABEL: LidoStat

NDC: 44577-704 | Form: CREAM
Manufacturer: Clinical Therapeutic Solutions
Category: otc | Type: HUMAN OTC DRUG LABEL
Date: 20231105

ACTIVE INGREDIENTS: LIDOCAINE HYDROCHLORIDE 40 mg/1 g
INACTIVE INGREDIENTS: ALOE VERA LEAF; WATER; C13-14 ISOPARAFFIN; CETYL ALCOHOL; DIMETHICONE; ETHYLHEXYLGLYCERIN; LAURETH-7; DIMETHYL SULFONE; PHENOXYETHANOL; POLYSORBATE 20; STEARIC ACID; TROLAMINE; UREA

LidoStat CREAM

Active Ingredient

Lidocaine HCL 4%

Purpose

External Anesthetic

Uses:

For temporary relief of pain and itching caused by minor skin irritations.

Warnings:

For external use only.

Do not use

on children under 2 years of age unless directed by a physician.

When using this product

avoid contact with eyes Use only as directed. Do not use in large quantities, particularly over raw surfaces or blistered areas.

Stop use and ask a doctor if:

- symptoms persist for more than seven days, or clear up and occur again within a few days.
- redness, irritation, swelling, pain or other symptoms increase

Keep out of reach of children.

If swallowed, consult a physician.

Directions:

For adults and children two-years or older, apply externally to the affected area. Do not use more than three to four times per day.

Children under 2 years of age: Ask a doctor.

Other information:

Store at room temperature (68-77ºF) (20º-25ºC)

Other Ingredients:

Aloe Barbadensis Leaf (Aloe Vera Gel) Juice, Aqua (Deionized Water), Bin Vinyl Dimethicone/Dimethicone Copolymer, C13-14 Isoparaffin, Cetyl Alcohol, Dimethicone, Ethylhexylglycerin, Laureth-7, Methylsulfonylmethane (MSM), Phenoxyethanol, Polyacrylamide, Polysorbate-20, Stearic Acid, Triethanolamine, Urea.

Question or Comments?

Please visit www.BakoCTS.com

LidoStatTM Cream

Distributed by: CLINICAL THERAPEUTIC SOLUTIONS A Part of bako's Integrated Physician Solution PO Box 1257, Wall, NJ 07719 732.894.9450 •
www.BakoCTS.com

PACKAGE LABEL

LidoStat CREAM

Lidocaine HCI 4% In a 20% Urea Vehicle MEDICAL STRENGTH PAIN CREAM

PENETRATING FORMULA

Dipensed Only by Physicians

NET WT. 2.0 oz (56 g)

LOT:

EXP: